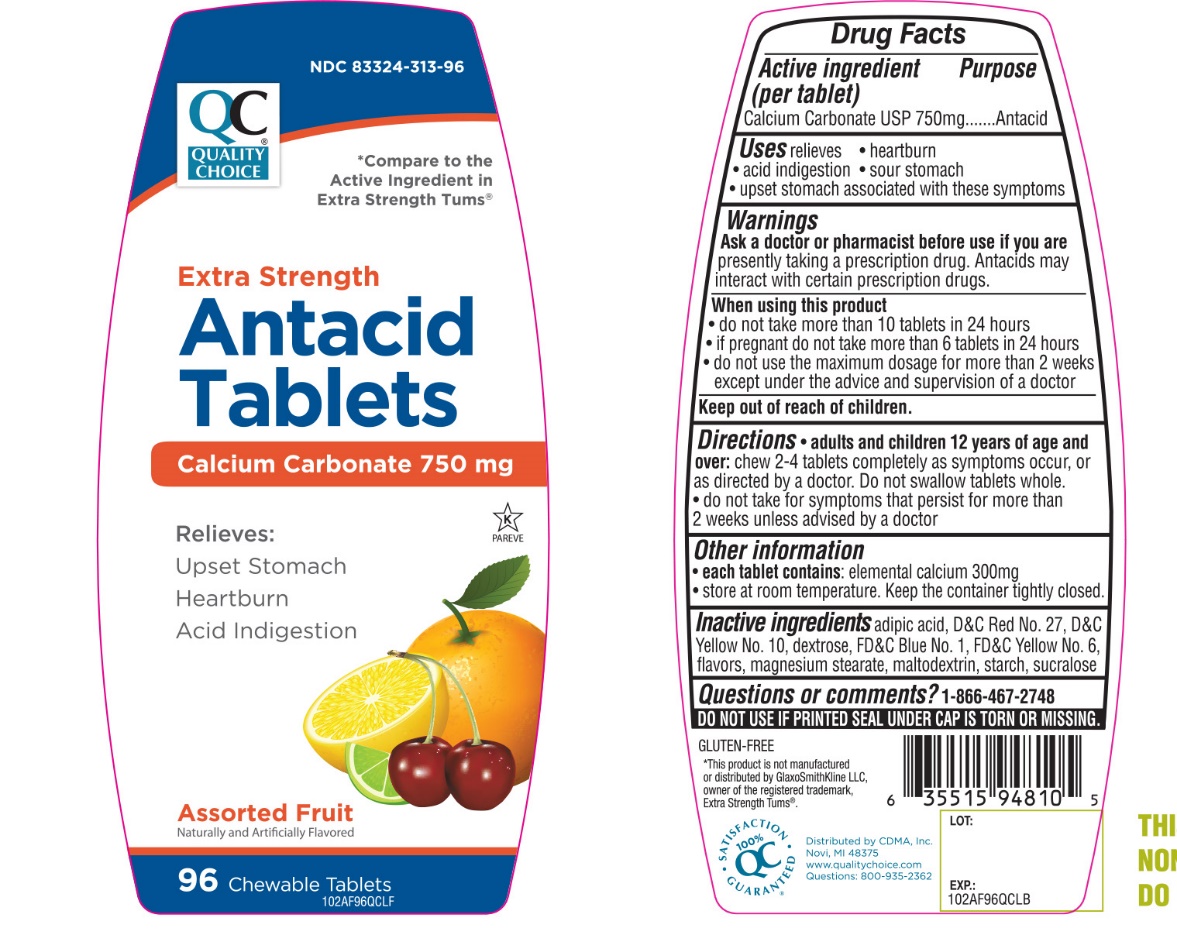 DRUG LABEL: Quality Choice

NDC: 83324-313 | Form: TABLET, CHEWABLE
Manufacturer: QUALITY CHOICE (Chain drug Marketing Assoiciation)
Category: otc | Type: HUMAN OTC DRUG LABEL
Date: 20251204

ACTIVE INGREDIENTS: CALCIUM CARBONATE 750 mg/1 1
INACTIVE INGREDIENTS: ADIPIC ACID; D&C RED NO. 27; D&C YELLOW NO. 10; DEXTROSE, UNSPECIFIED FORM; FD&C BLUE NO. 1; FD&C YELLOW NO. 6; MAGNESIUM STEARATE; MALTODEXTRIN; STARCH, CORN; SUCRALOSE

Quality Choice Extra Strength Assorted Fruit Antacid Tablets Drug Facts

Active ingredient (per tablet)

Calcium Carbonate USP 750mg

Purpose

Antacid

Uses

relieves

- heartburn
- sour stomach
- acid indigestion
- upset stomach associated with these symptoms

Warnings

Ask a doctor or pharmacist before use if you are

- presently taking a prescription drug. Antacids may interact with certain prescription drugs.

When using this product

- do not take more than 10 tablets in 24 hours
- if pregnant do not take more than 6 tablets in 24 hours
- do not use the maximum dosage for more than 2 weeks except under the advice and supervision of a doctor

Directions

- adults and children 12 years of ageand over: chew 2 - 4 tablets completely as symptoms occur, or as directed by a doctor. Do not swallow tablets whole.
- Do not take for symptoms that persist for more than 2 weeks unless advised by a doctor

Other information

- each tablet contains:calcium 300 mg
- store at room temperature. Keep the container tightly closed.

Inactive ingredients

adipic acid, D&C Red No. 27, D&C Yellow 10, dextrose, FD &C Blue No. 1, FD&C Yellow No. 6, flavors, magnesium stearate, maltodextrin, starch, sucrose.

Questions or comments?

1-866-467-2748

SAFETY SEALED. DO NOT USE IF PRINTED SEAL UNDER CAP IS TORN OR MISSING.

Principal Display Panel

*Compare to the Active Ingredient in Extra Strength Tums®

NDC 83324-313-96

Extra Strength

Antacid Tablets

Calcium Carbonate 750 mg

Relieves:

- Upset Stomach
- Heartburn
- Acid Indigestion

Assorted Fruit

Naturally and Artificially Flavored

K PAREVE

96 Chewable Tablets

GLUTEN FREE

100% QC SATISFACTION GUARANTEED

Distributed by: C.D.M.A. Inc.

Novi, MI 48375

www.qualitychoice.com

Questions: 800-935-2362

*This product is not manufactured or distributed by GlaxoSmithKline LLC, owner of the registered trademark, Extra Strength Tums®